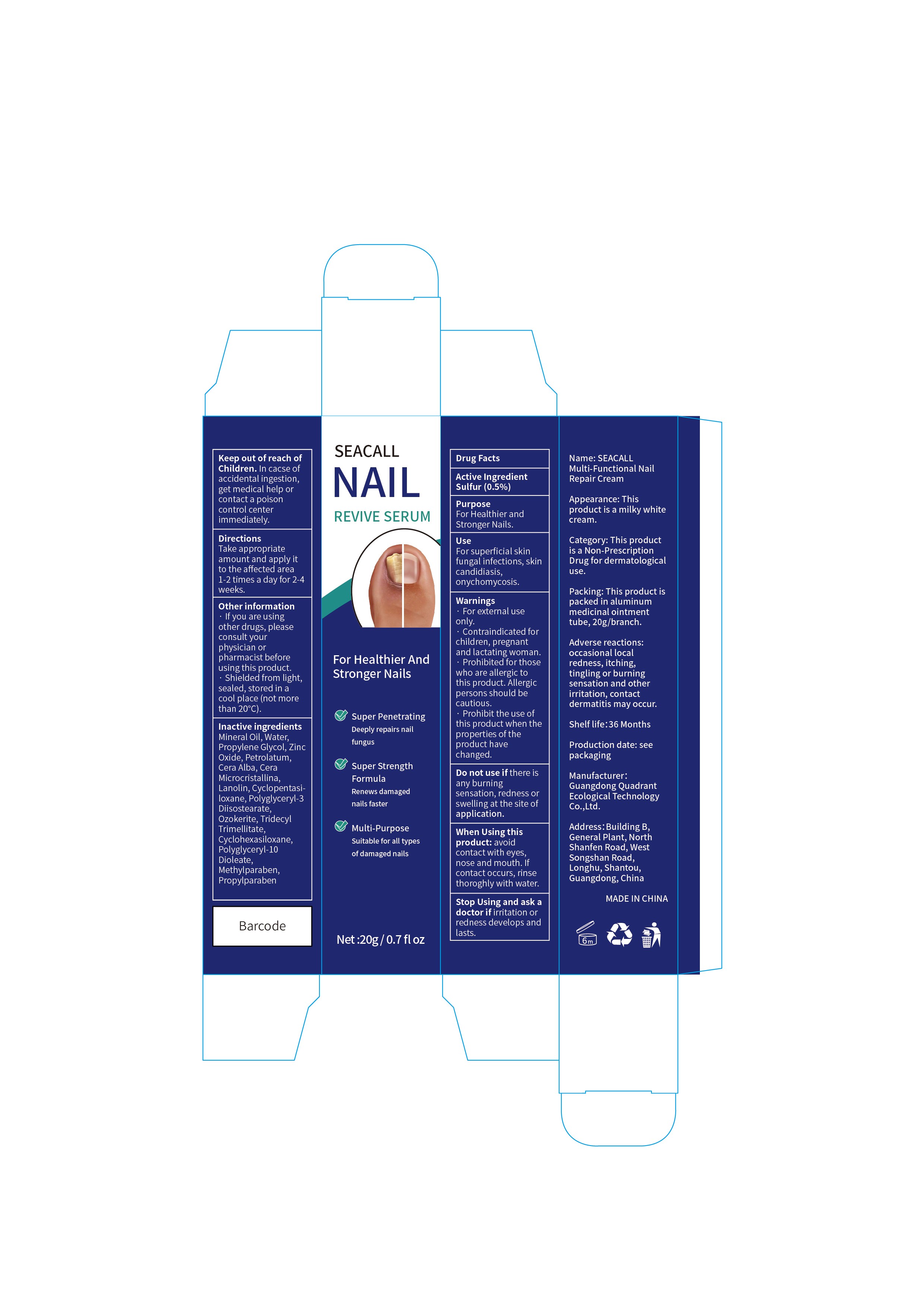 DRUG LABEL: SEACALL NAIL REVIVE SERUM
NDC: 76986-002 | Form: CREAM
Manufacturer: Guangdong Quadrant Ecological Technology Co., Ltd.
Category: otc | Type: HUMAN OTC DRUG LABEL
Date: 20251015

ACTIVE INGREDIENTS: SULFUR 0.5 g/100 g
INACTIVE INGREDIENTS: WHITE WAX; WATER; PETROLATUM; PROPYLPARABEN; LANOLIN; MINERAL OIL; PROPYLENE GLYCOL; ZINC OXIDE; ETHYLENE DISTEARAMIDE; CYCLOMETHICONE 5; POLYGLYCERYL-3 DIISOSTEARATE; CERESIN; TRIDECYL TRIMELLITATE; METHYLPARABEN; POLYGLYCERYL-10 DIOLEATE; CYCLOMETHICONE 6

76986-002 Active

Active Ingredient

Sulfur 0.5%

Purpose

For Healthier and Stronger Nails.

Use

For superficial skin fungal infections, skin candidiasis,onychomycosis.

Warnings

· For external use only.
· Contraindicated for children, pregnant and lactating woman.
· Prohibited for those who are allergic to this product. Allergic persons should be cautious.
· Prohibit the use of this product when the properties of the product have changed.

Do not use if there is any burning sensation, redness or swelling at the site of application.

When Using

When Using this product: avoid contact with eyes, nose and mouth. If contact occurs, rinse thoroghly with water.

Stop Use

Stop Using and ask a doctor if irritation or redness develops and lasts.

Ask Doctor

Stop Using and ask a doctor if irritation or redness develops and lasts.

Keep Oot Of Reach Of Children

Keep out of reach of Children. In cacse of accidental ingestion, get medical help or contact a poison control center immediately.

Directions

Take appropriate amount and apply it to the affected area 1-2 times a day for 2-4 weeks.

Other information

If you are using other drugs, please consult your physician or pharmacist before using this product.
Shielded from light, sealed, stored in a cool place (not more than 20℃).

Inactive ingredients

Mineral Oil, Water, Propylene Glycol, Zinc Oxide, Petrolatum, Cera Alba, Cera Microcristallina, Lanolin, Cyclopentasi loxane, Polyglyceryl-3 Diisostearate, Ozokerite, Tridecyl Trimellitate, Cyclohexasiloxane, Polyglyceryl-10 Dioleate, Methylparaben, Propylparaben